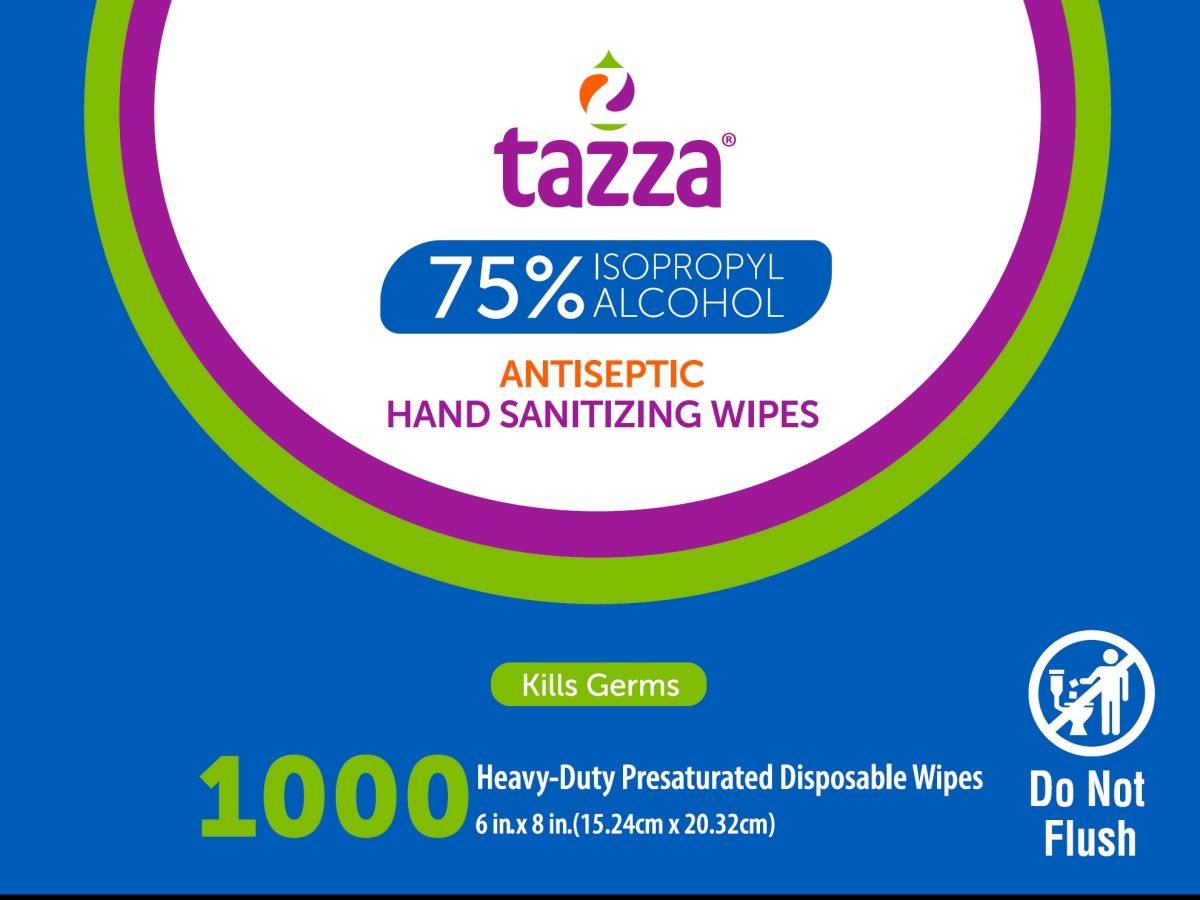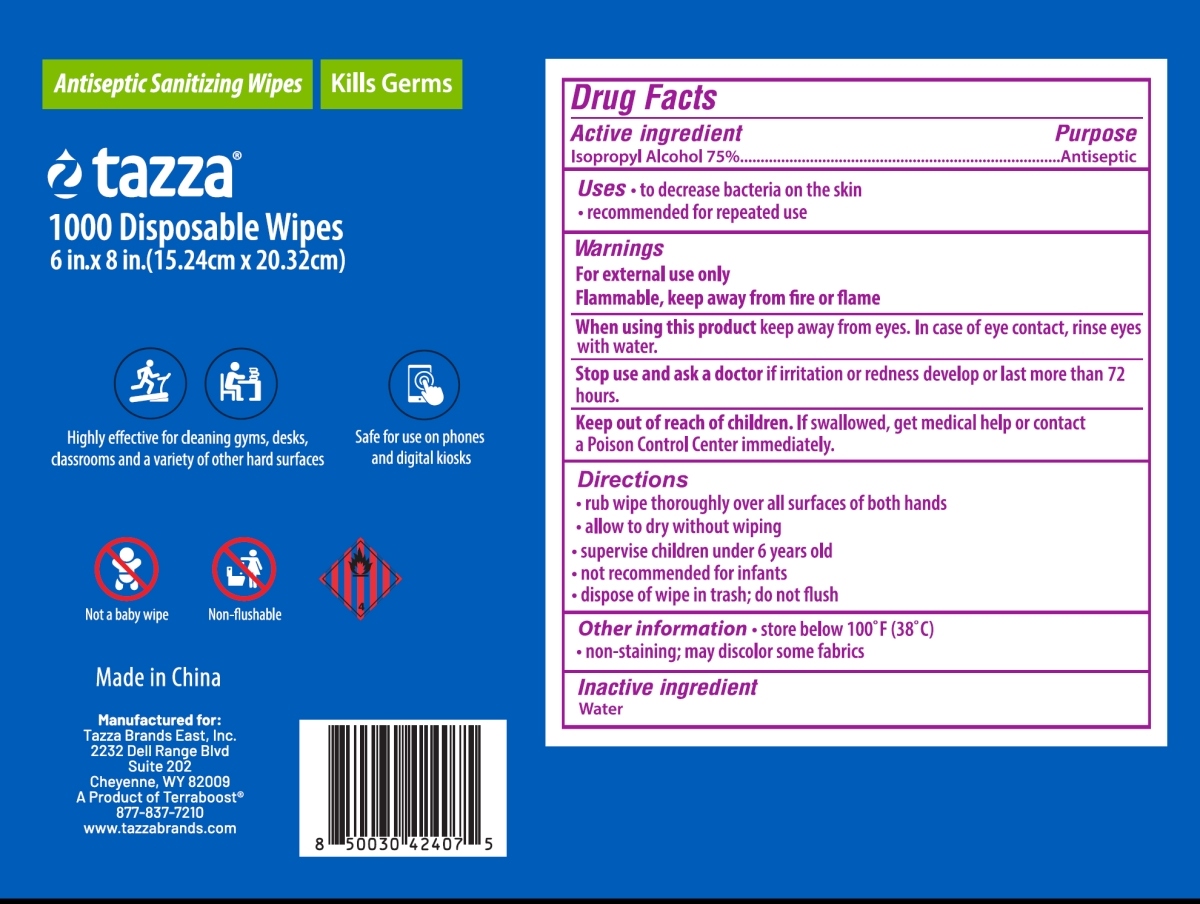 DRUG LABEL: Tazza Antiseptic Hand Wipes
NDC: 76370-0012 | Form: CLOTH
Manufacturer: Tazza Brands East Inc.
Category: otc | Type: HUMAN OTC DRUG LABEL
Date: 20251217

ACTIVE INGREDIENTS: ISOPROPYL ALCOHOL 75 mL/100 mL
INACTIVE INGREDIENTS: WATER

76370-0012 Tazza Antiseptic Wipes (75% IPA)

Drug Facts

Active ingredient

Isopropyl Alcohol 75%

Purpose

Antiseptic

Uses

- to decrease bacteria on the skin
- recommended for repeated use

Warnings

For external use only

Flammable, keep away from fire or flame

When using this product keep away from eyes. In case of eye contact, rinse eyes with water.

Stop use and ask a doctor if irritation or redness develop or last more than 72 hours.

Keep out of reach of children. If swallowed, get medical help or contact a Poison Control Center immediately.

Directions

- rub wipe thoroughly over all surfaces of both hands
- allow to dry without wiping
- supervise children under 6 years old
- not recommended for infants
- dispose of wipe in trash; do not flush

Other information

- store below 100°F (38°C)
- non-staining; may discolor some fabrics

Inactive ingredient

Water

Made in China

Manufactured for:
Tazza Brands East, Inc.
2232 Dell Range Blvd
Suite 202
Cheyenne, WY 82009
A Product of Terraboost®
877-837-7210
www.tazzabrands.com

PACKAGE LABEL

tazza®

75% ISOPROPYL ALCOHOL

ANTISEPTIC HAND SANITIZING WIPES

Kills germs

1000 Heavy Duty Presaturated Disposable Wipes

6 in x 8 in (15.24cm x 20.32cm)

NDC: 76370-0012-0